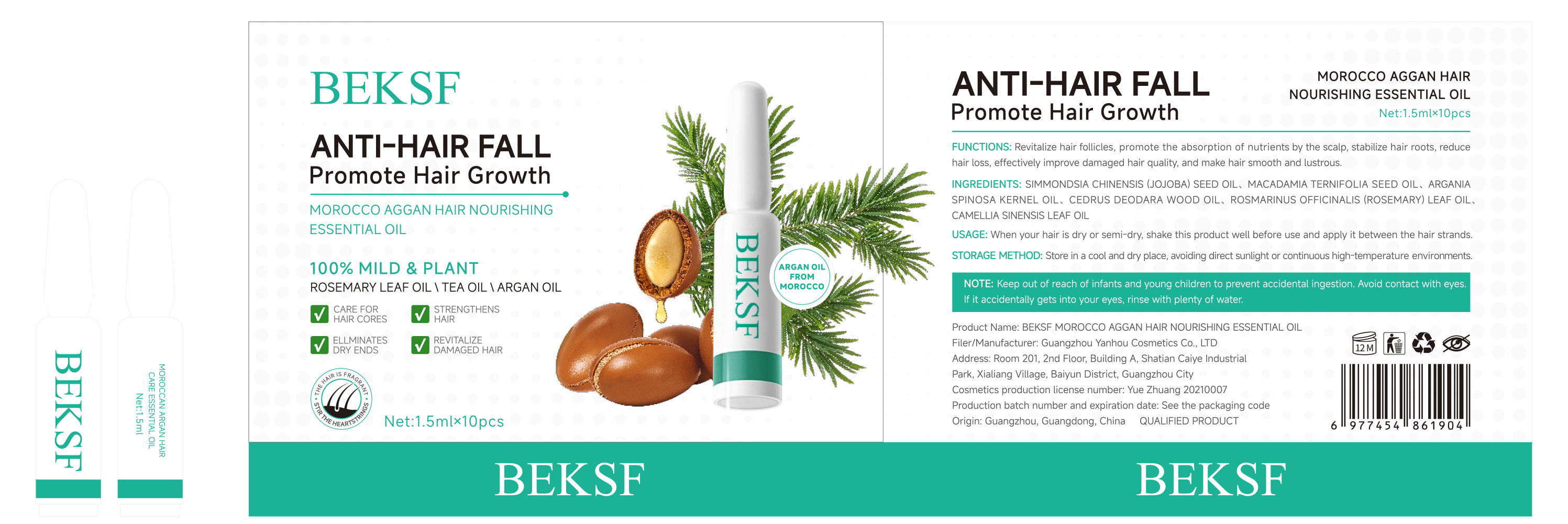 DRUG LABEL: BEKSF MOROCCO AGGAN HAIR NOURISHING ESSENTIAL Oil
NDC: 85977-002 | Form: OIL
Manufacturer: Guangzhou Yanhou Cosmetics Co., Ltd.
Category: otc | Type: HUMAN OTC DRUG LABEL
Date: 20251027

ACTIVE INGREDIENTS: ROSMARINUS OFFICINALIS (ROSEMARY) LEAF OIL 0.02 g/1 mL
INACTIVE INGREDIENTS: MACADAMIA TERNIFOLIA SEED OIL; SIMMONDSIA CHINENSIS (JOJOBA) SEED OIL; ARGANIA SPINOSA KERNEL OIL; WHITE TEA; CEDRUS DEODARA WOOD OIL

85977-002 BEKSF MOROCCO AGGAN HAIR NOURISHING ESSENTIAL OIL

ACTIVE INGREDIENT

ROSEMARY OIL

PURPOSE

Promote Hair Growth

INDICATIONS AND USAGE

FUNCTlONS: Revitalize hair folicles, promote the absorption of nutrients by the scalp, stabilize hair roots, reduce hair loss, effectively improve damaged hair quality, and make hair smooth and lustrous.

WARNINGS

NOTE: Keep out of reach of infants and young children to prevent accidental ingestion. Avoid contact with eyes.
If it accidentally gets into your eyes, rinse with plenty of water.

Children and pregnant women should not use it

WHEN USING

NOTE: Keep out of reach of infants and young children to prevent accidental ingestion. Avoid contact with eyes.
If it accidentally gets into your eyes, rinse with plenty of water.

KEEP OUT OF REACH OF CHILDREN

Keep out of reach of infants and young children to prevent accidental ingestion

DOSAGE AND ADMINISTRATION

When your hair is dry or semi-dry, shake this product well before use and apply it between the hair strands.

INACTIVE INGREDIENT

CAMELLIA SINENSIS LEAF OIL
SIMMONDSIA CHINENSIS (JOJOBA) SEED OIL
MACADAMIA TERNIFOLIA SEED OIL
ARGANIA SPINOSA KERNEL OIL
CEDRUS DEODARA WOOD OIL